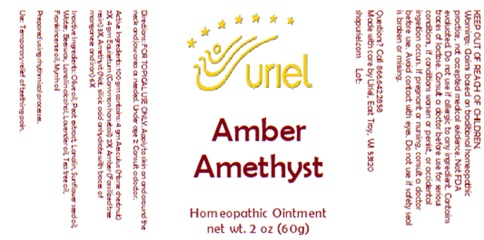 DRUG LABEL: Amber Amethyst
NDC: 48951-1408 | Form: OINTMENT
Manufacturer: Uriel Pharmacy, Inc
Category: homeopathic | Type: HUMAN OTC DRUG LABEL
Date: 20260112

ACTIVE INGREDIENTS: HORSE CHESTNUT 2 [hp_X]/1 g; AMBER 3 [hp_X]/1 g; EQUISETUM ARVENSE WHOLE 2 [hp_X]/1 g; SILICON DIOXIDE 6 [hp_X]/1 g
INACTIVE INGREDIENTS: LANOLIN; TEA TREE OIL; FRANKINCENSE OIL; SPHAGNUM SQUARROSUM PEAT; SUNFLOWER OIL; WATER; BEESWAX; LANOLIN ALCOHOL; LAVENDER OIL; OLIVE OIL; MYRRH OIL

Amber Amethyst

INDICATIONS AND USAGE

Directions: FOR TOPICAL USE ONLY.

DOSAGE AND ADMINISTRATION

Apply to skin on and around the neck and jaw area as needed. Under age 2: Consult a doctor.

ACTIVE INGREDIENT

Active Ingredients: 100 gm contains: 4 gm Aesculus (Horse chestnut) 2X, 4 gm Equisetum (Common horsetail) 2X; Amber (Fossilized tree resin) 3X, Amethyst (Nat. silicic acid anhydrate with traces of manganese and iron) 6X

INACTIVE INGREDIENT

Inactive Ingredients: Olive oil, Peat extract, Lanolin, Sunflower seed oil, Water, Beeswax, Lanolin alcohol, Lavender oil, Tea tree oil, Frankincense oil, Myrrh oil

Prepared using rhythmical processes.

PURPOSE

Use: Temporary relief of teething pain.

KEEP OUT OF REACH OF CHILDREN.

WARNINGS

Warnings: Claims based on traditional homeopathic practice, not accepted medical evidence. Not FDA evaluated. Do not use if allergic to any ingredient. Contains traces of lactose. Consult a doctor before use for serious conditions, if conditions worsen or persist, or accidental ingestion occurs. If pregnant or nursing, consult a doctor before use. Avoid contact with eyes. Do not use if safety seal is broken or missing.

Questions? Call 866.642.2858
Made with care by Uriel, East Troy, WI 53120
shopuriel.com Lot: